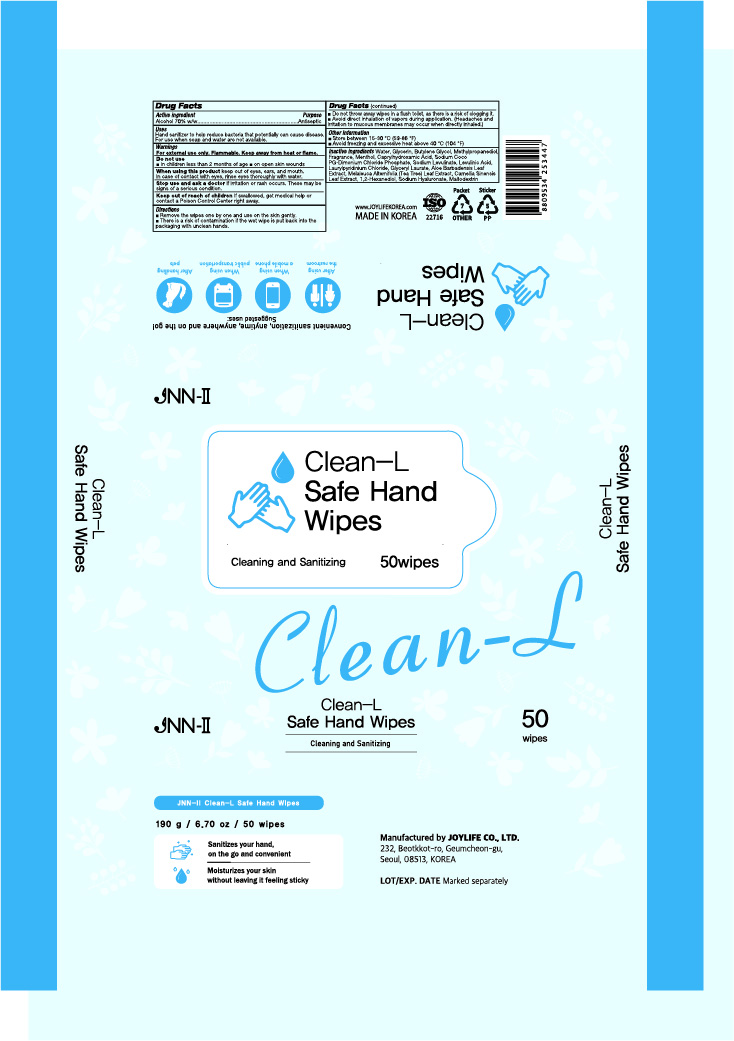 DRUG LABEL: JNN-II Clean-L Safe Hand Wipes
NDC: 78424-700 | Form: CLOTH
Manufacturer: JOY LIFE Co., Ltd.
Category: otc | Type: HUMAN OTC DRUG LABEL
Date: 20200924

ACTIVE INGREDIENTS: ALCOHOL 2.66 g/1 1
INACTIVE INGREDIENTS: BUTYLENE GLYCOL; METHYLPROPANEDIOL; MENTHOL; MELALEUCA ALTERNIFOLIA LEAF; GREEN TEA LEAF; MALTODEXTRIN; WATER; GLYCERIN; SODIUM LEVULINATE; GLYCERYL LAURATE; ALOE VERA LEAF; 1,2-HEXANEDIOL; HYALURONATE SODIUM; CAPRYLHYDROXAMIC ACID; LEVULINIC ACID; LAURYLPYRIDINIUM CHLORIDE

JOY LIFE Co., Ltd. | JNN-II Clean-L Safe Hand Wipes | 50 wipes

PACKAGE LABEL

Active ingredient

Alcohol 70% w/w

Purpose

Antiseptic

Warnings

For external use only. Flammable. Keep away from heat or flame.

Do not use

■ in children less than 2 months of age ■ on open skin wounds

When using this product

keep out of eyes, ears, and mouth. In case of contact with eyes, rinse eyes thoroughly with water.

Stop use and ask a doctor

if irritation or rash occurs. These may be signs of a serious condition.

Keep out of reach of children

If swallowed, get medical help or contact a Poison Control Center right away.

Directions

■ Remove the wipes one by one and use on the skin gently.

■ There is a risk of contamination if the wet wipe is put back into the packaging with unclean hands.

■ Do not throw away wipes in a flush toilet, as there is a risk of clogging it.

■ Avoid direct inhalation of vapors during application. (Headaches and irritation to mucous membranes may occur when directly inhaled.)

Other information

■ Store between 15-30 °C (59-86 °F)

■ Avoid freezing and excessive heat above 40 °C (104 °F)

Inactive ingredients

Water, Glycerin, Butylene Glycol, Methylpropanediol, Fragrance, Menthol, Caprylhydroxamic Acid, Sodium Coco PG-Dimonium Chloride Phosphate, Sodium Levulinate, Levulinic Acid, Laurylpyridinium Chloride, Glyceryl Laurate, Aloe Barbadensis Leaf Extract, Melaleuca Alternifolia (Tea Tree) Leaf Extract, Camellia Sinensis Leaf Extract, 1,2-Hexanediol, Sodium Hyaluronate, Maltodextrin